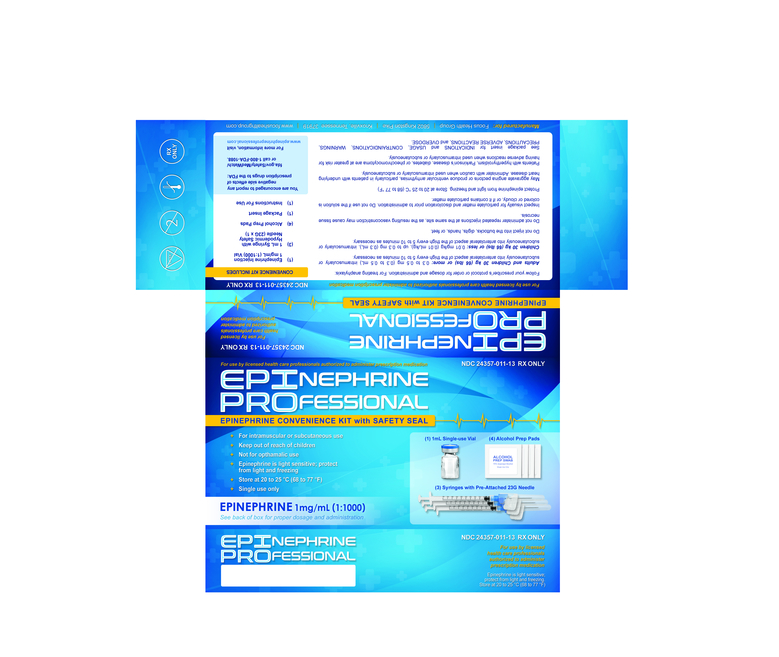 DRUG LABEL: Epinephrine Professional
NDC: 24357-011 | Form: KIT | Route: SUBCUTANEOUS
Manufacturer: Focus Health Group
Category: prescription | Type: HUMAN PRESCRIPTION DRUG LABEL
Date: 20260211

ACTIVE INGREDIENTS: EPINEPHRINE 1 mg/1 mL; ISOPROPYL ALCOHOL 0.7 mL/1 mL
INACTIVE INGREDIENTS: TARTARIC ACID 2.25 mg/1 mL; HYDROCHLORIC ACID; SODIUM HYDROXIDE 1 mg/1 mL; WATER; EDETATE DISODIUM 0.2 mg/1 mL; SODIUM METABISULFITE 0.457 mg/1 mL; SODIUM CHLORIDE 7.3 mg/1 mL; WATER

Epinephrine Professional Convenience Kit

DOSAGE AND ADMINISTRATION

For treating anaphylaxis:

Adults and Children 30 kg (66 lbs) or more: 0.3 to 0.5 mg (0.3 to 0.5 ml) intramuscularly or subcutaneously into anterolateral aspect of the thigh every 5 to 10 minutes as necessary.

Children 30 kg (66 lbs) or less: 0.01 mg/kg (0.01 ml/kg), up to 0.3 mg (0.3 ml), intramuscularly or subcutaneously into anterolateral aspect of the thigh every 5 to 10 minutes as necessary.